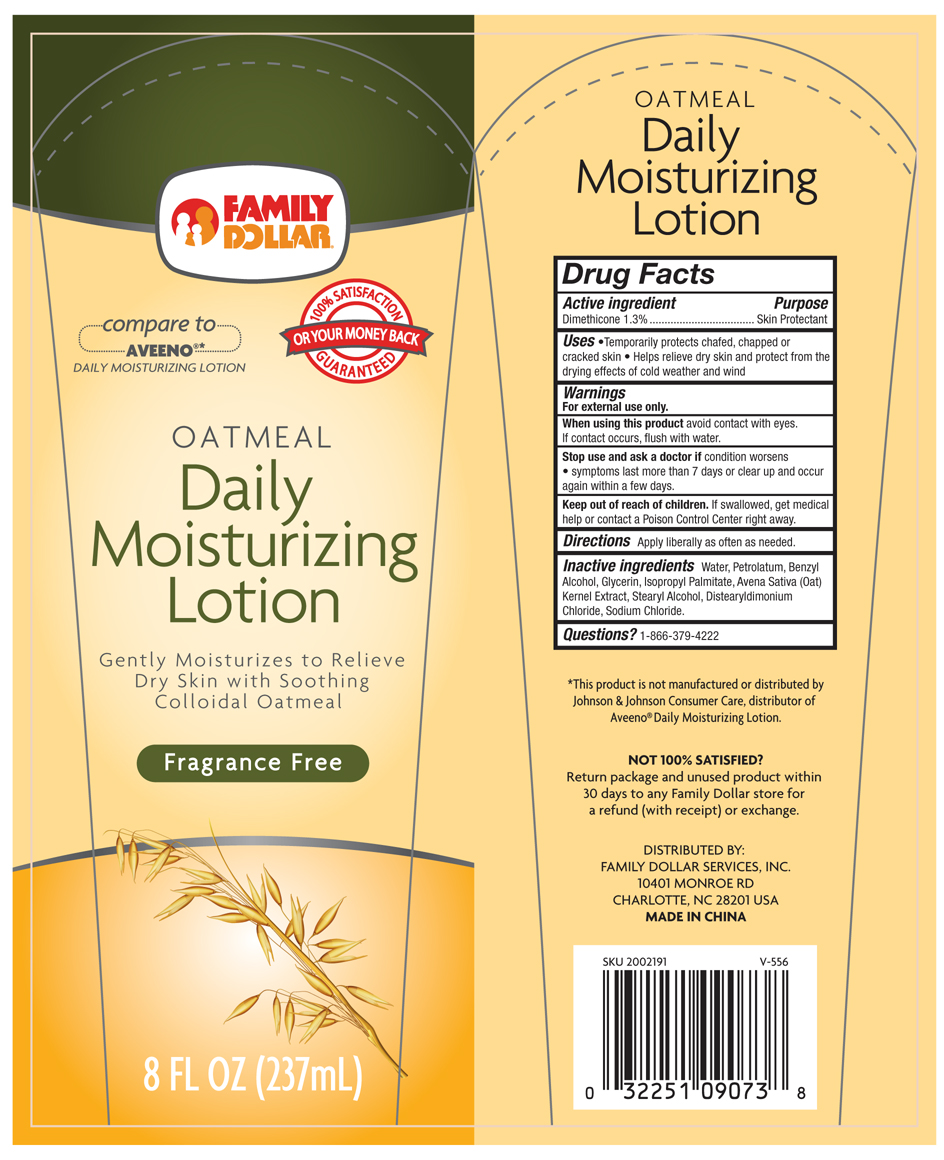 DRUG LABEL: Oatmeal Daily Moisturizing
NDC: 42669-111 | Form: LOTION
Manufacturer: Davion, Inc
Category: otc | Type: HUMAN OTC DRUG LABEL
Date: 20140331

ACTIVE INGREDIENTS: Dimethicone 13 mg/1 g
INACTIVE INGREDIENTS: AVENA SATIVA FLOWERING TOP; Benzyl Alcohol; Stearyl Alcohol; Distearyldimonium Chloride; Glycerin; Isopropyl Palmitate; Petrolatum; Sodium Chloride; Water

Oatmeal Daily Moisturizing Lotion

Drug Facts

Active ingredients

Dimethicone (1.3%)

Purpose

Skin Protectant

Uses

- Temporarily protects chafed, chapped or cracked skin.
- Helps relieve dry skin and protect from the drying effects of cold weather and wind.

Warnings

For external use only

When using this product avoid contact with eyes.

If contact occurs, flush with water.

Stop use and ask a doctor if condition worsens.

- symptoms last more than 7 days or clear up and occur again within a few days.

Keep out of reach of children. If swallowed, get medical help or contact a Poison Control Center right away

Directions

Apply liberally as often as needed.

Inactive ingredients

Water, Petrolatum, Benzyl Alcohol, Glycerin, Isopropyl Palmitate, Avena Sativa (Oat) Kernel Extract, Stearyl Alcohol, Distearyldimonium Chloride, Sodium Chloride

Questions?

1-866-379-4222

*This product is not manufactured or distributed by Johnson & Johnson Consumer Care, distributor of Aveeno ® Daily Mositurizing Lotion.

NOT 100% SATISFIED?

Return package and unused product within 30 days to any Family Dollar store for a refund (with receipt) or exchange.

Distributed by:
FAMILY DOLLAR SERVICES, INC.
10401 MONROE RD
CHARLOTTE, NC 28201 USA
MADE IN CHINA

PRINCIPAL DISPLAY PANEL - 226 g Tube Label

OATMEAL Daily Moisturizing Lotion

Gently Moisturizes to Relieve Dry Skin with Soothing Collodial Oatmeal

Fragrance Free

8 oz. (237 mL)